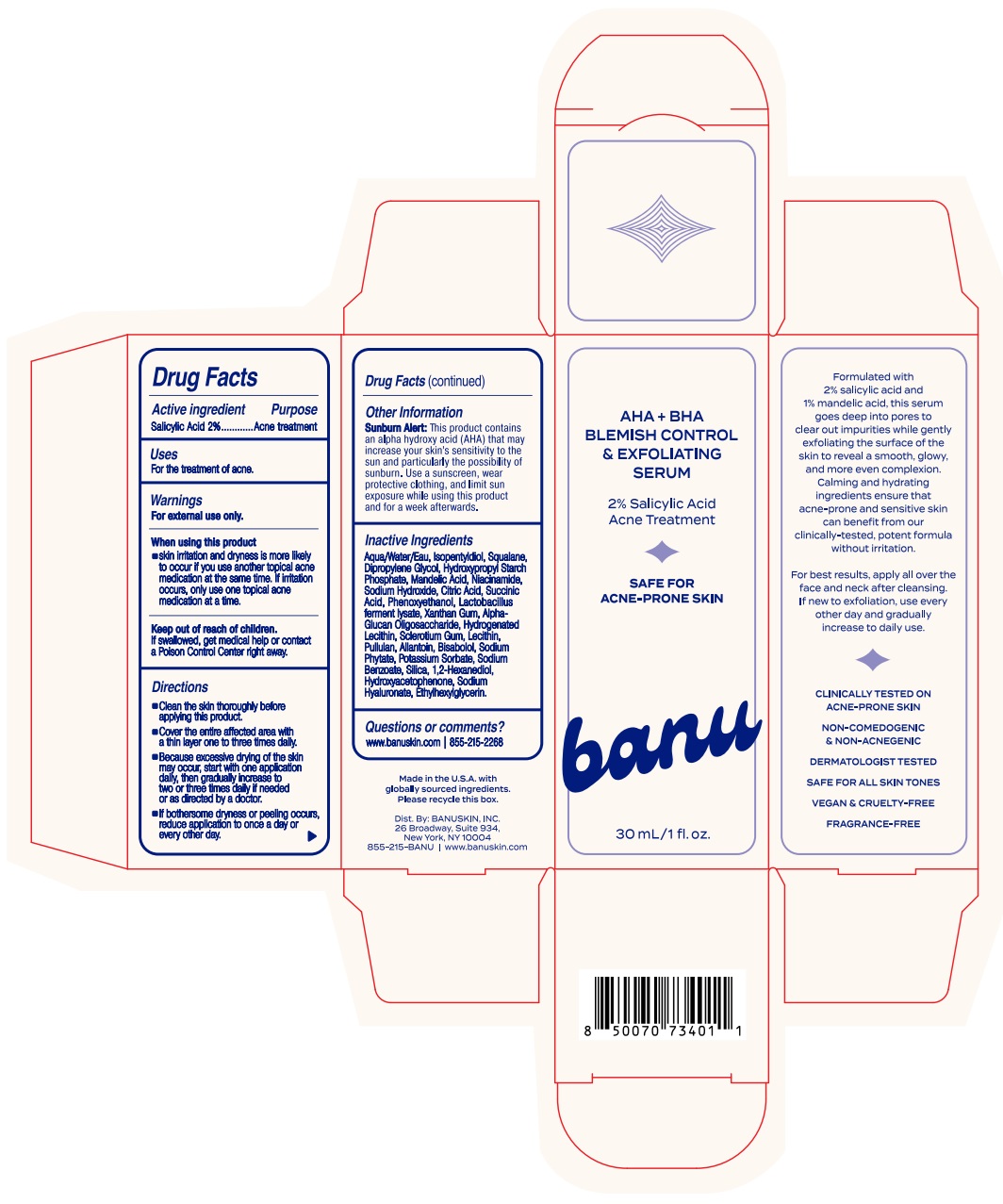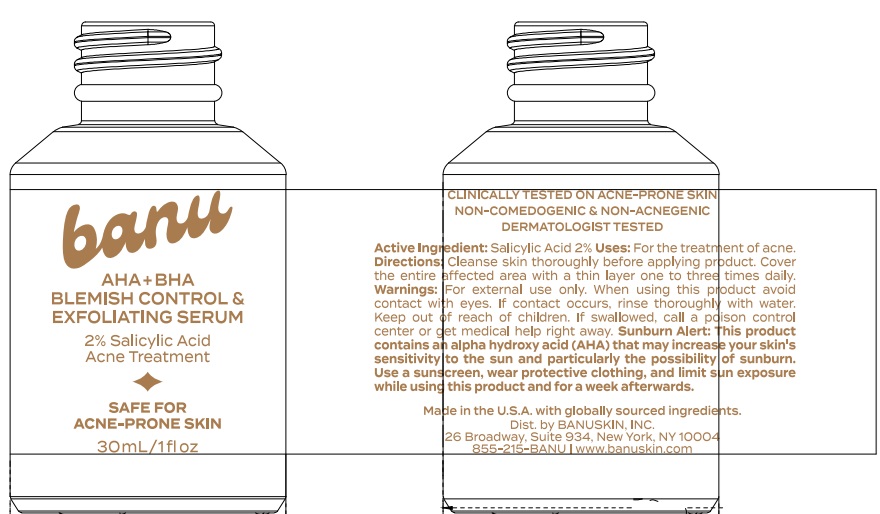 DRUG LABEL: AHA BHA Blemish Control and Exfoliating Serum
NDC: 85439-0101 | Form: LIQUID
Manufacturer: Banuskin, Inc.
Category: otc | Type: HUMAN OTC DRUG LABEL
Date: 20250403

ACTIVE INGREDIENTS: SALICYLIC ACID 2 g/100 mL
INACTIVE INGREDIENTS: NIACINAMIDE; CITRIC ACID; XANTHAN GUM; PHENOXYETHANOL; HYDROXYACETOPHENONE; ISOPENTYLDIOL; SQUALANE; HYDROXYPROPYL STARCH; SODIUM HYDROXIDE; PULLULAN; BISABOLOL; POTASSIUM SORBATE; ALPHA-GLUCAN OLIGOSACCHARIDE; SODIUM BENZOATE; SILICON DIOXIDE; SODIUM HYALURONATE; WATER; MANDELIC ACID; SODIUM PHYTATE; 1,2-HEXANEDIOL; DIPROPYLENE GLYCOL; SUCCINIC ACID; SCLEROTIUM GUM; ALLANTOIN; ETHYLHEXYLGLYCERIN

AHA + BHA Blemish Control & Exfoliating Serum

Active ingredient

Salicylic Acid 2.0%

Purpose

Acne Treatment

Uses

For the treatment of acne

Warnings

For external use only

When using this product • skin irritation and dryness is more likely to occur if you use another topical acne medication at the same time. If irritation occurs, only use one topical acne medication at a time.

Keep out of reach of children.

If swallowed, get medical help or contact a Poison Control Center right away.

Direction

- Cleanse skin thoroughly before applying product.
- Cover the entire affected area with a thin layer one to three times daily.
- Because excessive drying of the skin may occur, start with one application daily, then gradually increase to two or three times daily if needed or as directed by a doctor.
- if bothersome dryness or peeling occurs, reduce application to once a day or every other day.

Other Information

Sunburn Alert: This product contains an alpha hydroxy acid (AHA) that may increase your skin's sensitivity to the sun and particularly the possibility of sunburn. Use a sunscreen, wear protective clothing, and limit sun exposure while using this product and for a week afterwards.

Inactive Ingredient

Aqua/Water/Eau, Isopentyldiol, Squalane, Dipropylene Glycol, Hydroxypropyl Starch Phosphate, Mandelic Acid, Niacinamide, Sodium Hydroxide, Citric Acid, Succinic Acid, Phenoxyethanol, Lactobacillus ferment lysate, Xanthan Gum, Alpha-glucan oligosaccharide, Hydrogenated Lecithin, Sclerotium Gum, Lecithin, Pullulan, Allantoin, Bisabolol, Sodium Phytate, Potassium Sorbate, Sodium Benzoate, Silica, 1,2-Hexanediol, Hydroxyacetophenone, Sodium Hyaluronate, Ethylhexylglycerin.

Questions or comments?

www.banuskin.com

855-215-2268

DOSAGE AND ADMINISTRATION

Topical Liquid (Serum)

banu

AHA + BHA BLEMISH CONTROL & EXFOLIATING SERUM

2% Salicylic Acid

Acne Treatment

SAFE FOR ACNE-PRONE SKIN

30 mL/1 fl.oz

Labels

30 mL Bottle Carton

30 mL Bottle